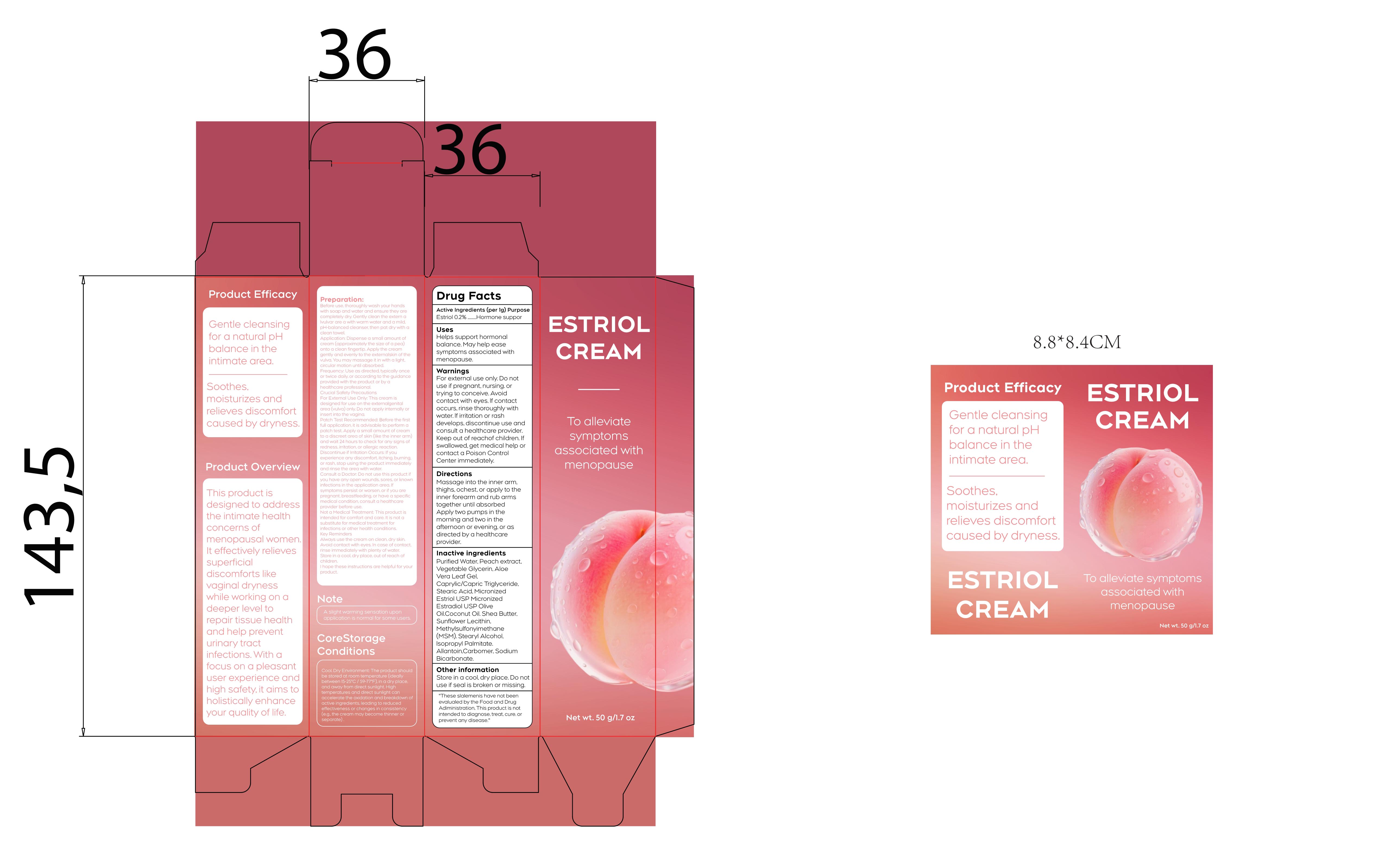 DRUG LABEL: ESTRIOL
NDC: 87255-006 | Form: CREAM
Manufacturer: Shenzhen Mengyue Technology Co., Ltd.
Category: otc | Type: HUMAN OTC DRUG LABEL
Date: 20251201

ACTIVE INGREDIENTS: ESTRIOL 0.2 g/100 g
INACTIVE INGREDIENTS: ALLANTOIN; CARBOMER; LECITHIN, SUNFLOWER; ESTRADIOL; ISOPROPYL PALMITATE; GLYCERIN; SODIUM BICARBONATE; COCONUT OIL; DIMETHYL SULFONE; TRICAPRIN; STEARIC ACID; OLIVE OIL; WATER; ALOE VERA LEAF; SHEA BUTTER; PEACH; STEARYL ALCOHOL

006 ESTRIOL CREAM

ACTIVE INGREDIENT

Estradiol 0.2%

PURPOSE

Hormone suppor

Uses

Helps support hormonal balance. May help ease symptoms associated with menopause.

Warnings

For external use only. Do not use if pregnant, nursing. or trying to conceive. Avoid contact with eyes. If contact occurs,rinse thoroughly with water. If irritation or rash develops, discontinue use and consult a healthcare provider.Keep out of reachof children. If swallowed, get medical help or contact a Poison Control Center immediately.

Do not use if pregnant, nursing. or trying to conceive.

WHEN USING

Avoid contact with eyes. If contact occurs,rinse thoroughly with water.

STOP USE

If irritation or rash develops, discontinue use and consult a healthcare provider.

Keep out of reachof children.

Directions

Massage into the inner arm, thighs,ochest,or apply to the inner forearm and rub arms together until absorbed Apply two pumps in the morning and two in the afternoon or evening, or as directed by a healthcare provider.

STORAGE AND HANDLING

CoreStorage

Conditions

Cool. Dry Environment: The product should be stored at room temperature (ideally between 15-25℃ / 59-77°F). in a dry place.and away from direct sunlight.High temperatures and direct sunlight can accelerate the oxidation and breakdown of active ingredients. leading to reduced effectiveness or changes in consistency (e.g.. the cream may become thinner or separate).

Other information

Store in a cool, dry place. Do not use if seal is broken or missing.

"These slalemenis have not been evalualed by the Food and Drug Adiministration, This product is not intended to diagnose, treat, cure. or prevent any disease."

Inactive ingredients

Purified Water, Peach extract.Vegetable Glycerin, Aloe Vera Leaf Gel,Caprylic/Capric Triglyceride.Stearic Acid, Micronized Estriol USP Micronized Estradiol USP Olive Oil.Coconut Oil. Shea Butter, Sunflower Lecithin.Methylsulfonyimethane (MSM). Stearyl Alcohol, Isopropyl Palmitate.Allantoin,Carbomer, Sodium Bicarbonate.